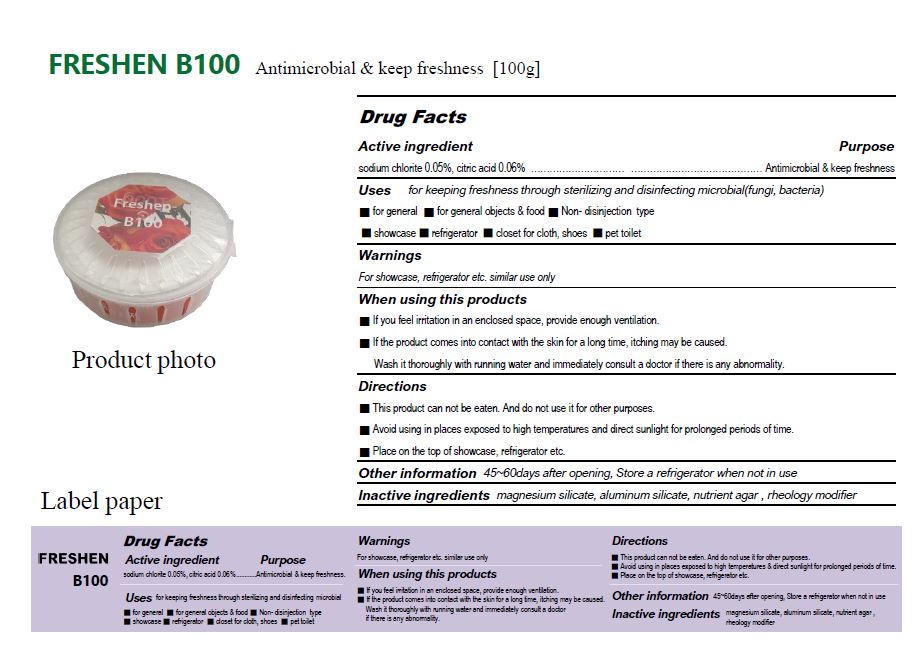 DRUG LABEL: B100
NDC: 77130-0004 | Form: POWDER
Manufacturer: Sejin E&P Co., Ltd.
Category: otc | Type: HUMAN OTC DRUG LABEL
Date: 20220217

ACTIVE INGREDIENTS: CITRIC ACID MONOHYDRATE 0.06 g/100 g; SODIUM CHLORITE 0.05 g/100 g
INACTIVE INGREDIENTS: MAGNESIUM SILICATE; ALUMINUM SILICATE

Drug Facts

ACTIVE INGREDIENT

sodium chlorite 0.05%

citric acid 0.06%

INACTIVE INGREDIENT

magnesium silicate, aluminum silicate, nurient agar, rheology modifier

PURPOSE

for keeping freshness through sterilizing and disinfecting microbial(fungi, bacteria)

KEEP OUT OF REACH OF THE CHILDREN

INDICATIONS AND USAGE

This product can not be eaten. And do not use it for other purposes

Avoid using in places exposed to high temperatures and direct sunlight for prolonged periods of time.

Put or Inserted in employee ID case, handbag, wallet, pocket or mask storage case.

WARNINGS

If you feel irritation in an enclosed space, provide enough ventilation

If the product comes into contact with the skin for a long time, itching may be caused.
Wash it thoroughly with running water and immediately consult a doctor if there is any abnormality.

DOSAGE AND ADMINISTRATION

for keeping freshness through sterilizing and disinfecting microbial(fungi, bacteria)